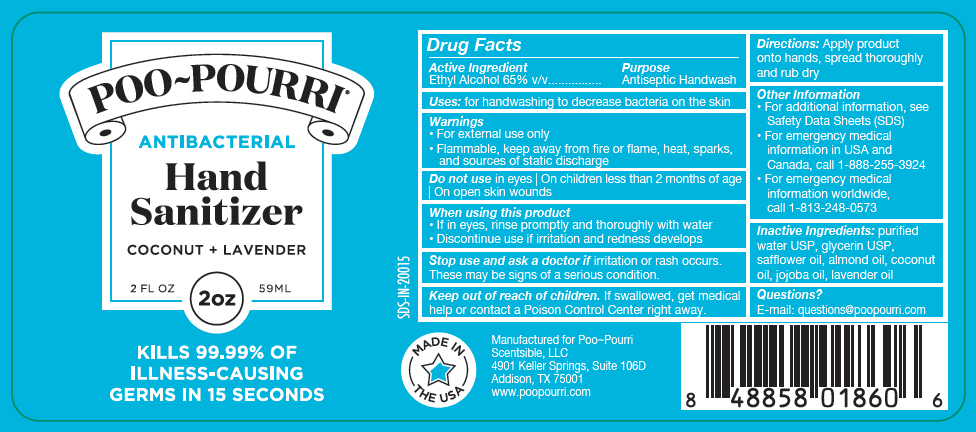 DRUG LABEL: Poo Pourri Antibacterial Hand Sanitizer - Coconut Plus Lavender
NDC: 73754-100 | Form: SPRAY
Manufacturer: Scentsible, LLC
Category: otc | Type: HUMAN OTC DRUG LABEL
Date: 20210719

ACTIVE INGREDIENTS: ALCOHOL 65 mL/100 mL
INACTIVE INGREDIENTS: Water; Glycerin; Safflower Oil; Almond Oil; Coconut Oil; Jojoba Oil; SPIKE LAVENDER OIL

Poo~Pourri® Antibacterial Hand Sanitizer - Coconut + Lavender

Drug Facts

Active Ingredient

Ethyl Alcohol 65% v/v

Purpose

Antiseptic Handwash

INDICATIONS AND USAGE

Uses: for handwashing to decrease bacteria on the skin

Warnings

- For external use only
- Flammable, keep away from fire or flame, heat, sparks, and sources of static discharge

Do not use in eyes | On children less than 2 months of age | On open skin wounds

When using this product

- If in eyes, rinse promptly and thoroughly with water
- Discontinue use if irritation and redness develops

Stop use and ask a doctor if irritation or rash occurs. These may be signs of a serious condition.

Keep out of reach of children. If swallowed, get medical help or contact a Poison Control Center right away.

Directions

Apply product onto hands, spread thoroughly and rub dry

Other Information

- For additional information, see Safety Data Sheets (SDS)
- For emergency medical information in USA and Canada, call 1-888-255-3924
- For emergency medical information worldwide, call 1-813-248-0573

Inactive Ingredients

purified water USP, glycerin USP, safflower oil, almond oil, coconut oil, jojoba oil, lavender oil

Questions?

E-mail: questions@poopourri.com

PRINCIPAL DISPLAY PANEL - 59 ML Bottle Label

POO~POURRI®

ANTIBACTERIAL

Hand
Sanitizer

COCONUT + LAVENDER

2 FL OZ
2oz
59ML

KILLS 99.99% OF
ILLNESS-CAUSING
GERMS IN 15 SECONDS